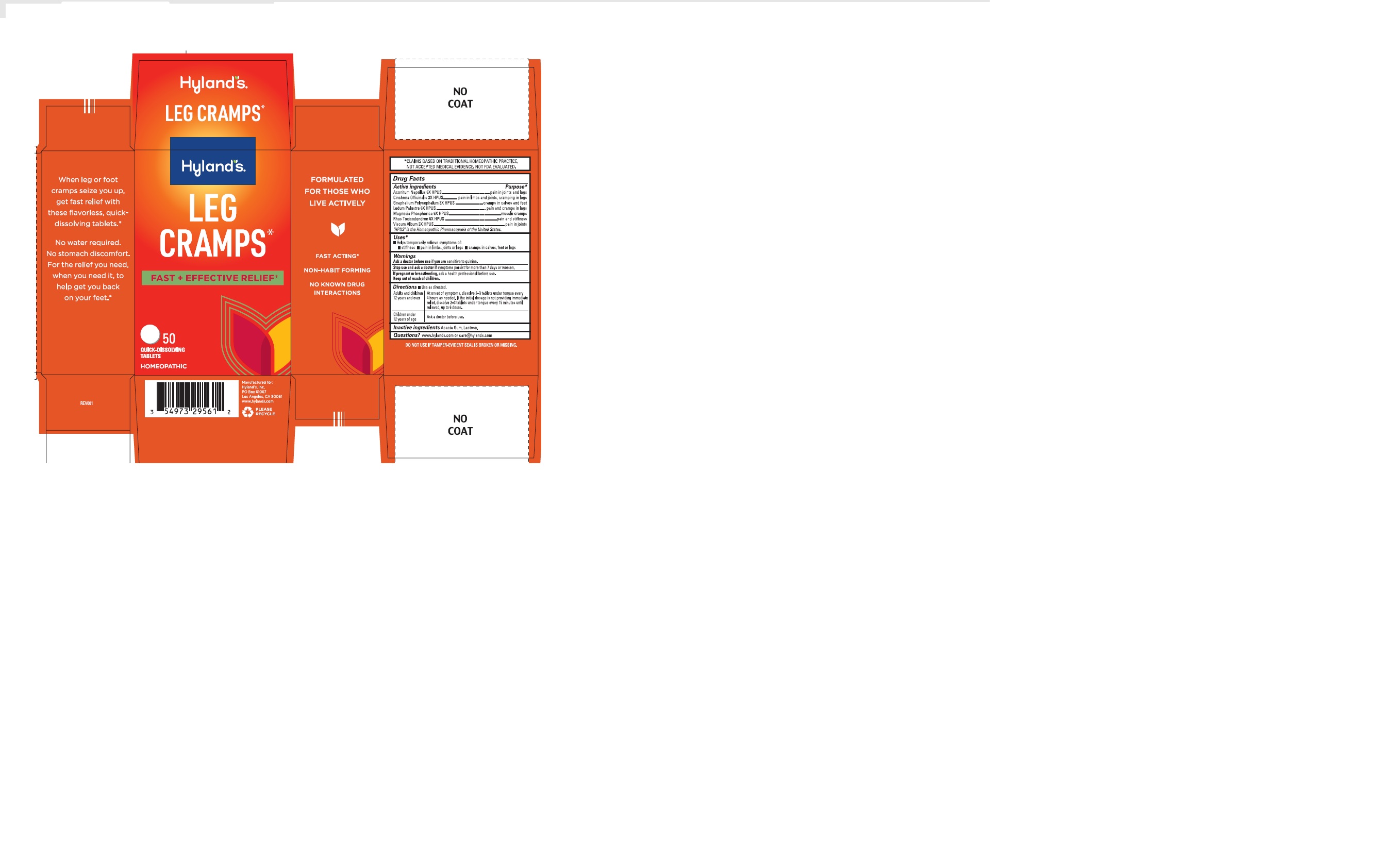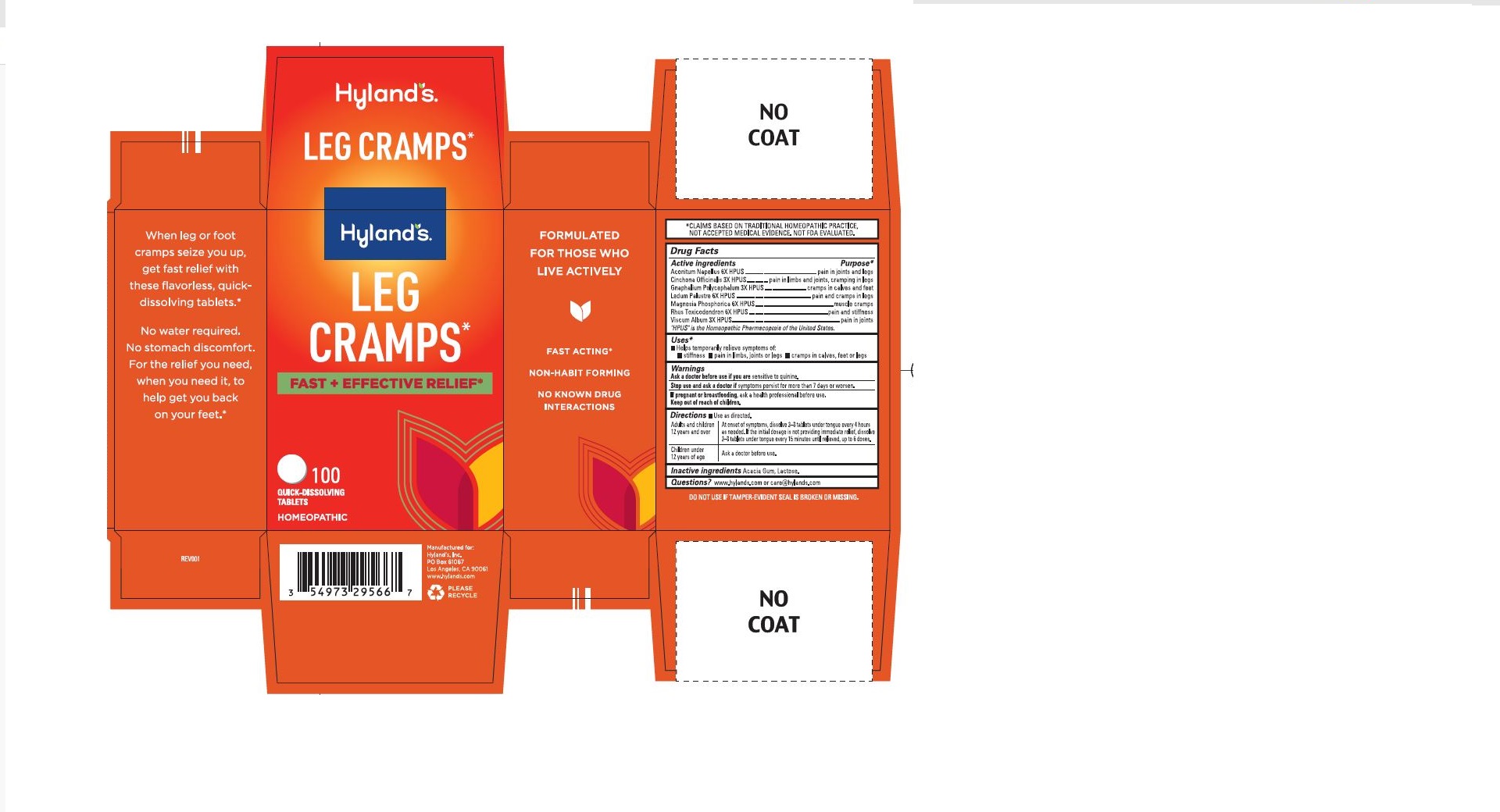 DRUG LABEL: LEG CRAMPS
NDC: 54973-2956 | Form: TABLET, SOLUBLE
Manufacturer: Hyland's Consumer Health Inc.
Category: homeopathic | Type: HUMAN OTC DRUG LABEL
Date: 20241023

ACTIVE INGREDIENTS: CINCHONA OFFICINALIS BARK 3 [hp_X]/1 1; ACONITUM NAPELLUS 6 [hp_X]/1 1; PSEUDOGNAPHALIUM OBTUSIFOLIUM 3 [hp_X]/1 1; LEDUM PALUSTRE TWIG 6 [hp_X]/1 1; MAGNESIUM PHOSPHATE, DIBASIC TRIHYDRATE 6 [hp_X]/1 1; TOXICODENDRON PUBESCENS LEAF 6 [hp_X]/1 1; VISCUM ALBUM FRUITING TOP 3 [hp_X]/1 1
INACTIVE INGREDIENTS: LACTOSE; ACACIA

Leg Cramps

PURPOSE

Temporarily relieves symptoms of: stiffness, pain in limbs, joints or legs, cramps in calves, feet or legs

Drug Facts

Active ingredients

Active ingredients | Purpose
Aconitum Napellus 6X HPUS | pains in joints and legs
Cinchona Officinalis 3X HPUS | pains in limbs and joints; cramping in legs
Gnaphalium Polycephalum 3X HPUS | cramps in calves and feet
Ledum Palustre 6X HPUS | pain and cramps in legs
Magnesia Phosphorica 6X HPUS | muscle cramps
Rhus Toxicodendron 6X HPUS | pain and stiffness
Viscum Album 3X HPUS | pains in joints

“HPUS” indicates that the active ingredients are in the official Homeopathic Pharmacopoeia of the United States.

Uses

■ Helps temporarily relieves the symptoms of:

■ stiffness ■ pain in limbs, joints or legs ■ cramps in calves, feet or legs

Warnings

Ask a doctor before use if you are

sensitive to quinine.

Stop use and ask a doctor

if symptoms persist for more than 7 days or worsen.

If pregnant or breastfeeding

Ask a health professional before use.

Directions

■ Use as directed.

Adults and children 12 years and over | Dissolve 2–3 tablets under tongue every 4 hours as needed. If the initial dosage is not providing immediate relief, dissolve 2–3 tablets under tongue every 15 minutes until relieved, up to 6 doses.
Children under 12 years of age | Ask a doctor before use.

Inactive ingredients

Acacia Gum, Lactose.

Questions?

www.hylands.com or care@hylands.com

Indications and Usage Dosage and Administration

Uses

- Temporarily relieves the symptoms of:
- stiffness 
- pain in limbs, joints or legs 
- cramps in calves, feet or legs

Directions

■ Temporarily relieves the symptoms of: ■ stiffness ■ pains in limbs ■ joints or legs ■ cramps in calves ■ feet or legs

Adults and children; 12 years and over | Dissolve 2–3 tablets under tongue every 4 hours. If the initial; dosage is not providing relief, dissolve 2–3 tablets under; tongue every 15 minutes, up to 6 doses.
Under 12 years of age | Consult a physician.

PRINCIPAL DISPLAY PANEL, Hyland's Leg Cramps Tablets 100 Count

Hyland's

LEG

CRAMPS

FAST + EFFECTIVE RELIEF*

100

QUICK-DISSOLVING

TABLETS

HOMEOPATHIC